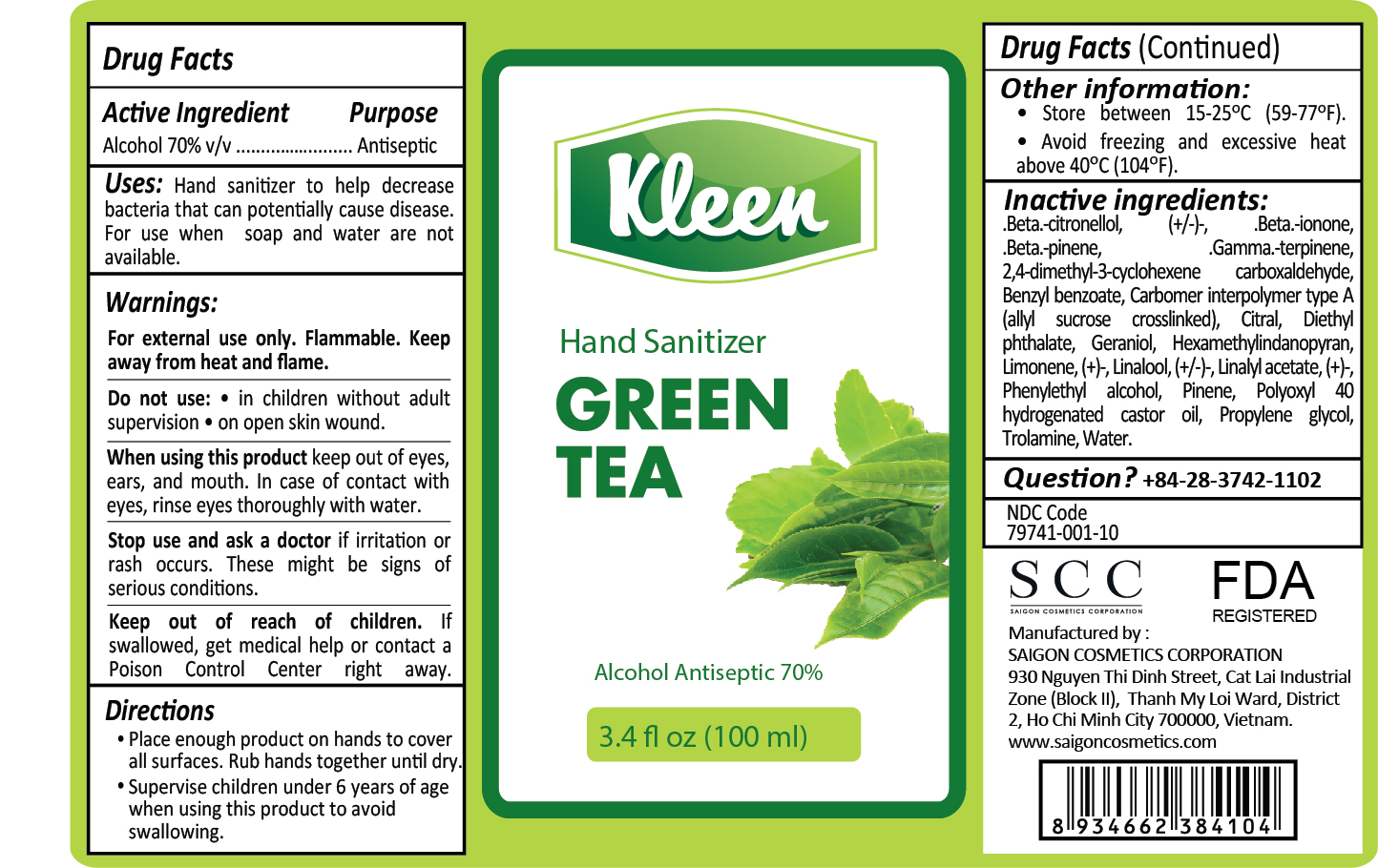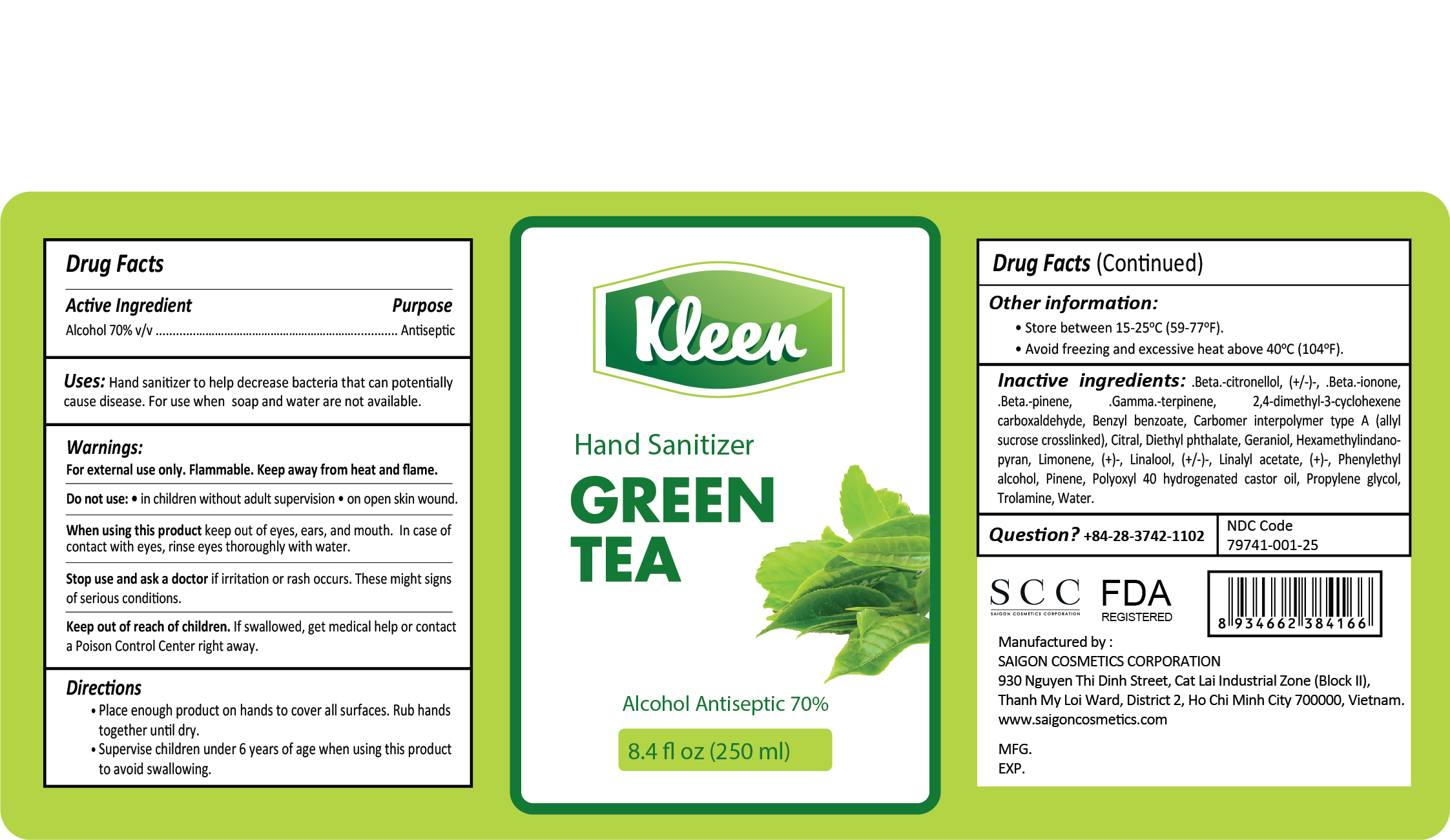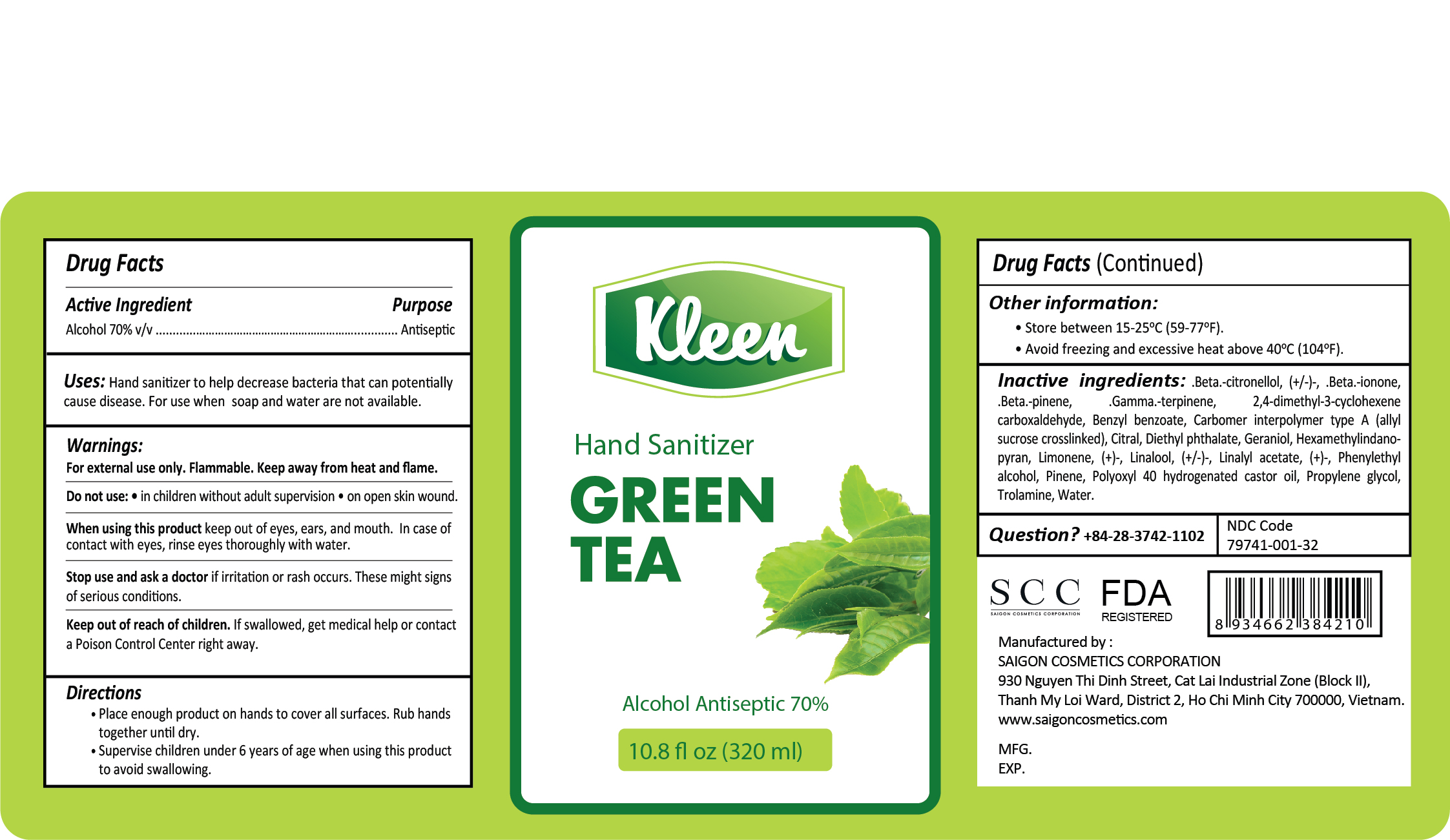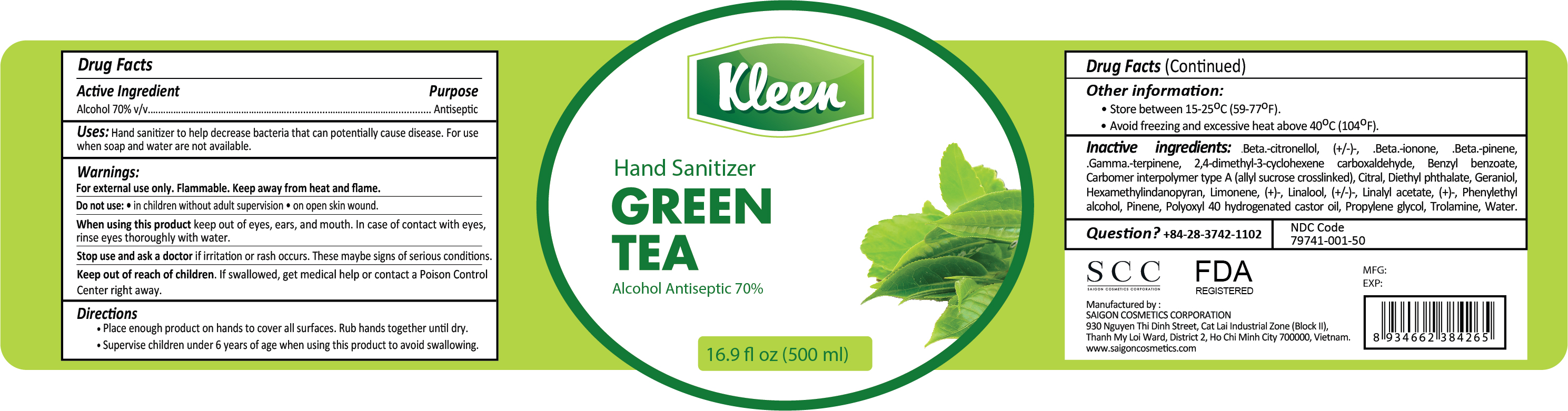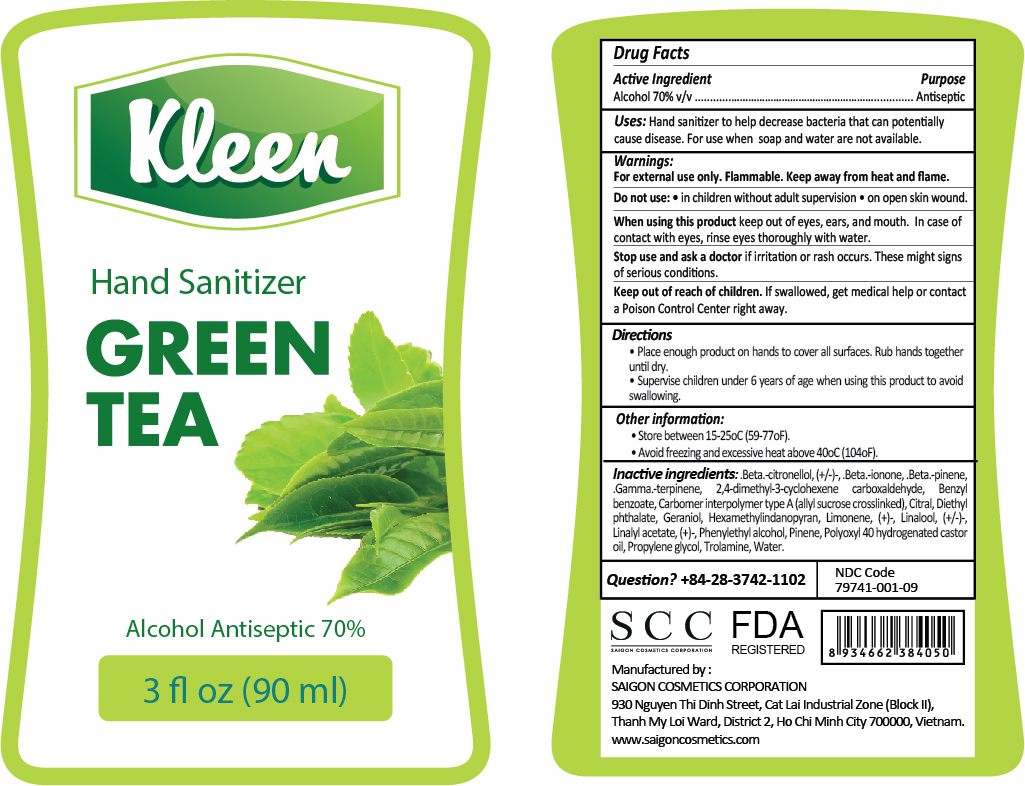 DRUG LABEL: KLEEN HAND SANITIZER GREEN TEA
NDC: 79741-001 | Form: GEL
Manufacturer: SAIGON COSMETICS CORPORATION
Category: otc | Type: HUMAN OTC DRUG LABEL
Date: 20200901

ACTIVE INGREDIENTS: ALCOHOL 70 mL/100 mL
INACTIVE INGREDIENTS: PHENYLETHYL ALCOHOL; LINALOOL, (+/-)-; .BETA.-IONONE; 2,4-DIMETHYL-3-CYCLOHEXENE CARBOXALDEHYDE; BENZYL BENZOATE; DIETHYL PHTHALATE; PINENE; GERANIOL; CITRAL; .GAMMA.-TERPINENE; POLYOXYL 40 HYDROGENATED CASTOR OIL; LIMONENE, (+)-; HEXAMETHYLINDANOPYRAN; WATER; CARBOMER INTERPOLYMER TYPE A (ALLYL SUCROSE CROSSLINKED); TROLAMINE; LINALYL ACETATE, (+)-; .BETA.-PINENE; PROPYLENE GLYCOL; .BETA.-CITRONELLOL, (+/-)-

ACTIVE INGREDIENT

Alcohol 70% v/v Purpose: Antiseptic

PURPOSE

Antiseptic, Hand Sanitizer

INDICATIONS AND USAGE

Hand sanitizer to help decrease bacteria that can potentially cause disease. For use when soap and water are not available.

WARNINGS

For external use only. Flammable. Keep away from heat and flame.

Do not use

- In children without aldult supervision
- On open skin wound

When using this product keep out of eyes, ears, and mouth. In case of contact with eyes, rinse eyes thoroughly with water.

Stop use and ask a doctor if irritation or rash occurs. These may be signs of serious conditions.

Keep out of reach of children. If swallowed, get medical help or contact a Poison Control Center right away.

Directions:

· Place enough product on hands to cover all surfaces. Rub hands together until dry.

· Supervise children under 6 years of age when using this product to avoid swallowing.

Other information:

- Store between 15-25oC (59-77oF)
- Avoid freezing and excessive heat above 40oC (104oF)

INACTIVE INGREDIENT

Beta-citronellol, (+/-)-, .Beta.-ionone, .Beta.-pinene, .Gamma.-terpinene, 2,4-demethyl-3-cyclohexene carboxaldehyde, Benzyl benzoate, Carbomer interpolymer type a (ally sucrose crosslinked), Citral,

Diethyl phthalate, Geraniol, Hexamethylindanopyran, Limonene, (+)-, Linalool, (+/-)-, Linalyl acetate, (+)-, Phenylethyl alcohol, Pinene, Polyoxyl 40 hydrogenated castor oil, Propylene glycol, Trolamine, Water.

QUESTIONS

+84-28-3742-1102